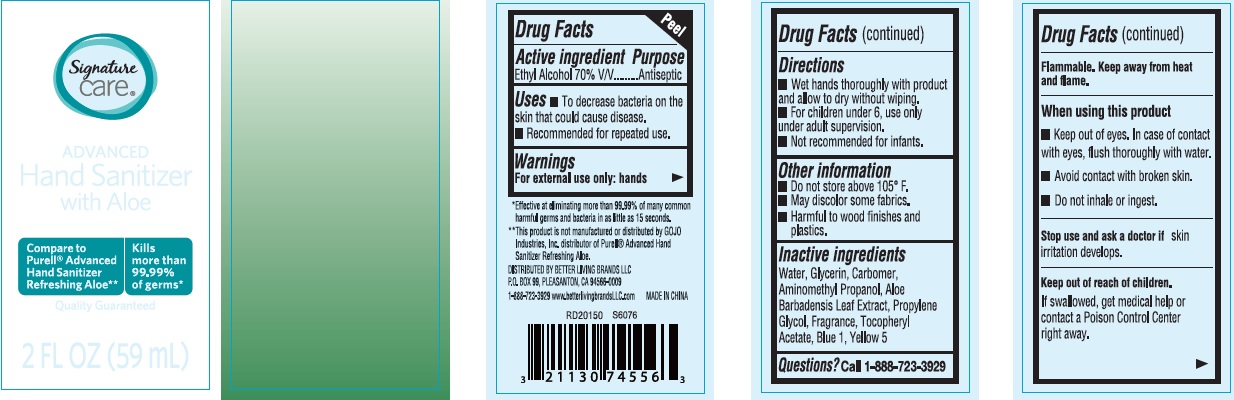 DRUG LABEL: Signature Care Advanced Hand Sanitizer with Aloe
NDC: 75262-006 | Form: LIQUID
Manufacturer: ZheJiang Eshine Cosmetic Co Ltd
Category: otc | Type: HUMAN OTC DRUG LABEL
Date: 20250112

ACTIVE INGREDIENTS: ALCOHOL 70 mL/100 mL
INACTIVE INGREDIENTS: WATER; PROPYLENE GLYCOL; ALOE VERA LEAF; AMINOMETHYLPROPANOL; GLYCERIN; .ALPHA.-TOCOPHEROL ACETATE, D-; FD&C BLUE NO. 1; FD&C YELLOW NO. 5

HAND SANITIZER

Active ingredient

Ethyl Alcohol 70% v/v

Purpose

Antiseptic

Use

- To decrease bacteria on the skin that could cause disease.
- Recommended for repeaed use.

Warnings

For external use only: hands

Flammable.Keep away from heat and flame.

When using this product

- Keep out of eyes. In case of contact with eyes, fllush thoroughly with water.
- Avoid contact with broken skin.
- Do not inhale or ingest.

Stop use and ask a doctor if

skin irritation develops.

Other Information

- Do not store above 105℉.
- May discolor some fabrics.
- Harmful to wood finisheds and plastics.

Keep out of reach of children.

If swallowed, get medical help or contact a Poison Control Center right away.

Directions

- Wet hands thoroughly with product and allow to dry without wiping.
- For hildren under 6, use only under adult supervision.
- Not recommended for infants.

Inactive ingredients

Water, Glycerin, Aloe Barbadensis Leaf Extract, Propylene Glycol, Fragrance, Tocopheryl Acetate, blue 1, Yellow 5

Questions? Call 1-888-723-3929